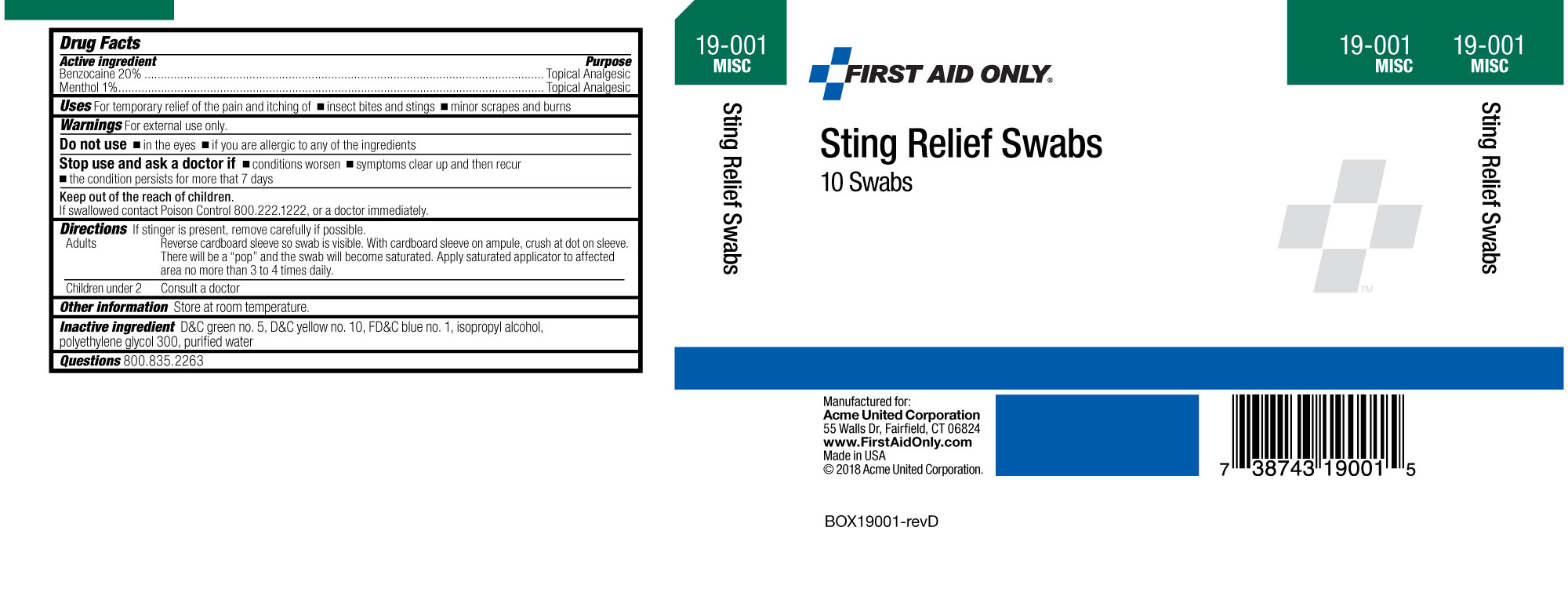 DRUG LABEL: First Aid Only Sting Relief
NDC: 0924-5250 | Form: SWAB
Manufacturer: Acme United Corporation
Category: otc | Type: HUMAN OTC DRUG LABEL
Date: 20241119

ACTIVE INGREDIENTS: BENZOCAINE 0.12 g/0.6 mL; MENTHOL 0.006 g/0.6 mL
INACTIVE INGREDIENTS: ISOPROPYL ALCOHOL; WATER; D&C GREEN NO. 5; D&C YELLOW NO. 10; FD&C BLUE NO. 1; POLYETHYLENE GLYCOL 300

First Aid Only Sting Relief Swabs

ACTIVE INGREDIENT

Benzocaine 20 percent
Menthol 1 percent

PURPOSE

Topical Analgesic

Topical Analgesic

Uses

For temporary relief of the pain and itching of

•insect bites and stings

•minor scrapes and burns

Warnings

For external use only.

Do not use

•in the eyes •if you are allergic to any of the ingredients

Stop use and ask a doctor if •conditions worsen •symptoms clear up and then recur •the condition persists for more than 7 days

Keep out of the reach of children

If swallowed, contact Poison Control 800.222.1222, or a doctor immediately.

DOSAGE AND ADMINISTRATION

Directions If stinger is present, remove carefully if possible.

Adults Reverse cardboard sleeve so swab is visible. With cardboard sleeve on ampile, crush at dot on sleeve.

There will be a "pop" and the swab will become saturated. Apply saturated applicator to the affected area no more than

3 to 4 times daily.

Children under 2 Consult a doctor.

Other Information

Store at room temperature.

INACTIVE INGREDIENT

D&C Green no. 5, D&C yellow no.10, FD&C blue no.1, isopropyl alcohol, polyethylene glycol 300, purified water

Questions 800.835.2263

PACKAGE LABEL

BOX19001-revD (002).jpg